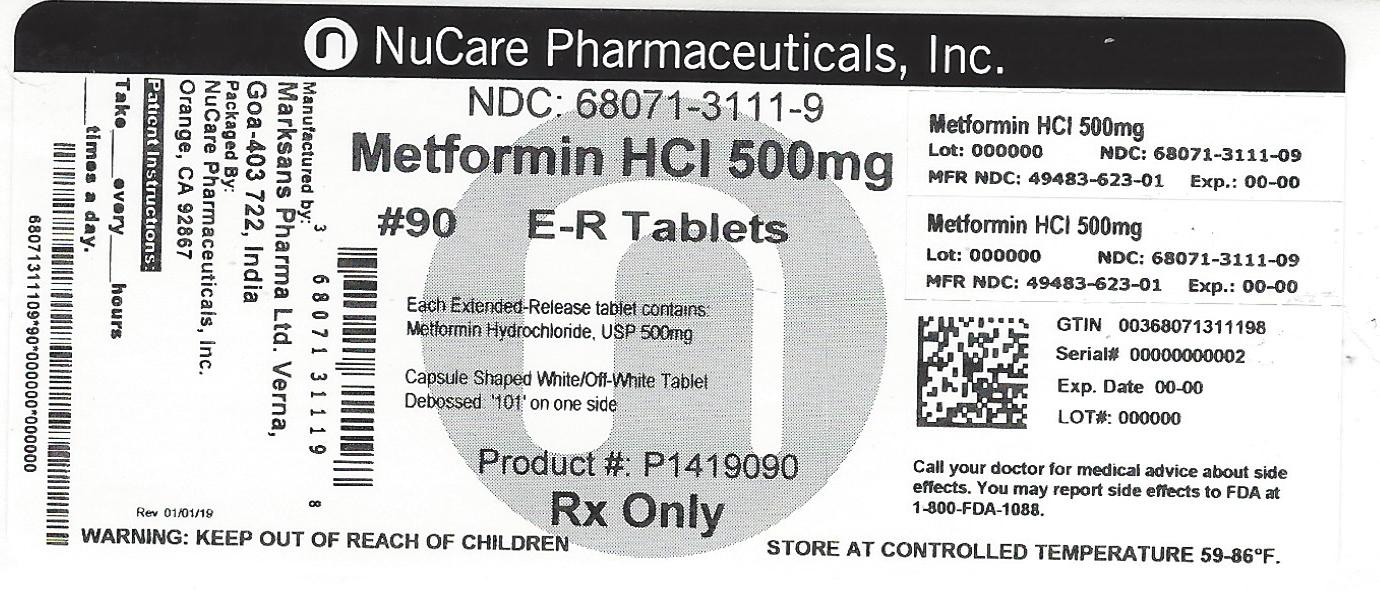 DRUG LABEL: METFORMIN HYDROCHLORIDE EXTENDED RELEASE
NDC: 68071-3111 | Form: TABLET, EXTENDED RELEASE
Manufacturer: NuCare Pharmaceuticals, Inc.
Category: prescription | Type: HUMAN PRESCRIPTION DRUG LABEL
Date: 20240719

ACTIVE INGREDIENTS: METFORMIN HYDROCHLORIDE 500 mg/1 1
INACTIVE INGREDIENTS: SILICON DIOXIDE; MAGNESIUM STEARATE; HYPROMELLOSE 2208 (100 MPA.S)

INDICATIONS AND USAGE

Metformin Hydrochloride Extended-Release Tablets, USP is indicated as an adjunct to diet and exercise to improve glycemic control in adults with type 2 diabetes mellitus.

HOW SUPPLIED

METFORMIN HYDROCHLORIDE EXTENDED-RELEASE TABLETS ARE SUPPLIED:

bottles of 30 NDC 68071-3111-3

bottles of 60 NDC 68071-3111-6

bottles of 90 NDC 68071-3111-9

bottles of 120 NDC 68071-3111-2

bottles of 180 NDC 68071-3111-8

500 MG - White to Off-White capsule shaped no score imprint code 101

DOSAGE AND ADMINISTRATION

There is no fixed dosage regimen for the management of hyperglycemia in patients with type 2 diabetes with metformin hydrochloride extended-release tablets or any other pharmacologic agent. Dosage of metformin hydrochloride extended-release tablets must be individualized on the basis of both effectiveness and tolerance, while not exceeding the maximum recommended daily doses. The maximum recommended daily dose of metformin hydrochloride extended-release tablets in adults is 2000 mg.
Metformin hydrochloride extended-release tablets should generally be given once daily with the evening meal. Metformin hydrochloride extended-release tablets should be started at a low dose, with gradual dose escalation, both to reduce gastrointestinal side effects and to permit identification of the minimum dose required for adequate glycemic control of the patient.
During treatment initiation and dose titration (see Recommended Dosing Schedule), fasting plasma glucose should be used to determine the therapeutic response to metformin hydrochloride extended-release tablets and identify the minimum effective dose for the patient. Thereafter, glycosylated hemoglobin should be measured at intervals of approximately three months. The therapeutic goal should be to decrease both fasting plasma glucose and glycosylated hemoglobin levels to normal or near normal by using the lowest effective dose of metformin hydrochloride extended-release tablets, either when used as monotherapy or in combination with sulfonylurea or insulin.
Monitoring of blood glucose and glycosylated hemoglobin will also permit detection of primary failure, i.e., inadequate lowering of blood glucose at the maximum recommended dose of medication, and secondary failure, i.e., loss of an adequate blood glucose lowering response after an initial period of effectiveness.
Short-term administration of metformin hydrochloride extended-release tablets may be sufficient during periods of transient loss of control in patients usually well-controlled on diet alone.
Metformin hydrochloride extended-release tablets must be swallowed whole and never crushed or chewed. Occasionally, the inactive ingredients of metformin hydrochloride extended-release tablets will be eliminated in the feces as a soft, hydrated mass. (See Patient information printed below.)
Recommended Dosing Schedule
Adults - In general, clinically significant responses are not seen at doses below 1500 mg per day. However, a lower recommended starting dose and gradually increased dosage is advised to minimize gastrointestinal symptoms.
The usual starting dose of metformin hydrochloride extended-release tablet is 500 mg once daily with the evening meal. Dosage increases should be made in increments of 500 mg weekly, up to a maximum of 2000 mg once daily with the evening meal. If glycemic control is not achieved on metformin hydrochloride extended-release tablets 2000 mg once daily, a trial of metformin hydrochloride extended-release tablets 1000 mg twice daily should be considered.
In a randomized trial, patients currently treated with metformin hydrochloride tablets were switched to metformin hydrochloride extended-release tablets. Results of this trial suggest that patients receiving metformin hydrochloride tablets treatment may be safely switched to metformin hydrochloride extended-release tablets once daily at the same total daily dose, up to 2000 mg once daily. Following a switch from metformin hydrochloride tablets to metformin hydrochloride extended-release tablets, glycemic control should be closely monitored and dosage adjustments made accordingly
Pediatrics – Safety and effectiveness of metformin hydrochloride extended-release tablets in pediatric patients have not been established.
Transfer From Other Antidiabetic Therapy
When transferring patients from standard oral hypoglycemic agents other than chlorpropamide to metformin hydrochloride extended-release tablets, no transition period generally is necessary. When transferring patients from chlorpropamide, care should be exercised during the first two weeks because of the prolonged retention of chlorpropamide in the body, leading to overlapping drug effects and possible hypoglycemia.
Concomitant Metformin Hydrochloride Extended-Release Tablets and Oral Sulfonylurea
Therapy in Adult Patients
If patients have not responded to four weeks of the maximum dose of metformin hydrochloride extended-release tablets monotherapy, consideration should be given to gradual addition of an oral sulfonylurea while continuing metformin hydrochloride extended-release tablets at the maximum dose, even if prior primary or secondary failure to a sulfonylurea has occurred. Clinical and pharmacokinetic drug-drug interaction data are currently available only for metformin plus glyburide (glibenclamide).
With concomitant metformin hydrochloride extended-release tablets and sulfonylurea therapy, the desired control of blood glucose may be obtained by adjusting the dose of each drug. However, attempts should be made to identify the minimum effective dose of each drug to achieve this goal. With concomitant metformin hydrochloride extended-release tablets and sulfonylurea therapy, the risk of hypoglycemia associated with sulfonylurea therapy continues and may be increased. Appropriate precautions should be taken. (See Package Insert of the respective sulfonylurea.)
If patients have not satisfactorily responded to one to three months of concomitant therapy with the maximum dose of metformin hydrochloride extended-release tablets and the maximum dose of an oral sulfonylurea, consider therapeutic alternatives including switching to insulin with or without metformin hydrochloride extended-release tablets.
Concomitant Metformin Hydrochloride Extended-Release Tablets and Insulin Therapy in Adult Patients

The current insulin dose should be continued upon initiation of metformin hydrochloride extended-release tablets therapy. Metformin hydrochloride extended-release tablets therapy should be initiated at 500 mg once daily in patients on insulin therapy. For patients not responding adequately, the dose of metformin hydrochloride extended-release tablets should be increased by 500 mg after approximately 1 week and by 500 mg every week thereafter until adequate glycemic control is achieved. The maximum recommended daily dose is 2000 mg for metformin hydrochloride extended-release tablets. It is recommended that the insulin dose be decreased by 10% to 25% when fasting plasma glucose concentrations decrease to less than 120 mg/dL in patients receiving concomitant insulin and metformin hydrochloride extended-release tablets. Further adjustment should be individualized based on glucose-lowering response.

Specific Patient Populations
Metformin hydrochloride extended-release tablets are not recommended for use in pregnancy. Metformin hydrochloride extended-release tablet is not recommended in pediatric patients (below the age of 17 years).
The initial and maintenance dosing of metformin hydrochloride extended-release tablets should be conservative in patients with advanced age, due to the potential for decreased renal function in this population. Any dosage adjustment should be based on a careful assessment of renal function. Generally, elderly, debilitated, and malnourished patients should not be titrated to the maximum dose of metformin hydrochloride extended-release tablets.
Monitoring of renal function is necessary to aid in prevention of lactic acidosis, particularly in the elderly.

WARNINGS

Lactic Acidosis:
Lactic acidosis is a rare, but serious, metabolic complication that can occur due to metformin accumulation during treatment with metformin hydrochloride extended-release tablets; when it occurs, it is fatal in approximately 50% of cases. Lactic acidosis may also occur in association with a number of pathophysiologic conditions, including diabetes mellitus, and whenever there is significant tissue hypoperfusion and hypoxemia. Lactic acidosis is characterized by elevated blood lactate levels (>5 mmol/L), decreased blood pH, electrolyte disturbances with an increased anion gap, and an increased lactate/pyruvate ratio. When metformin is implicated as the cause of lactic acidosis, metformin plasma levels >5 μg/mL are generally found.
The reported incidence of lactic acidosis in patients receiving metformin hydrochloride is very low (approximately 0.03 cases/1000 patient-years, with approximately 0.015 fatal cases/1000 patient-years). In more than 20,000 patient-years exposure to metformin in clinical trials, there were no reports of lactic acidosis. Reported cases have occurred primarily in diabetic patients with significant renal insufficiency, including both intrinsic renal disease and renal hypoperfusion, often in the setting of multiple concomitant medical/surgical problems and multiple concomitant medications. Patients with congestive heart failure requiring pharmacologic management, in particular those with unstable or acute congestive heart failure who are at risk of hypoperfusion and hypoxemia, are at increased risk of lactic acidosis. The risk of lactic acidosis increases with the degree of renal dysfunction and the patient's age. The risk of lactic acidosis may, therefore, be significantly decreased by regular monitoring of renal function in patients taking metformin hydrochloride extended-release tablets and by use of the minimum effective dose of metformin hydrochloride extended-release tablets. In particular, treatment of the elderly should be accompanied by careful monitoring of renal function. Metformin hydrochloride extended-release tablets treatment should not be initiated in patients ≥80 years of age unless measurement of creatinine clearance demonstrates that renal function is not
reduced, as these patients are more susceptible to developing lactic acidosis. In addition, metformin hydrochloride extended-release tablets should be promptly withheld in the presence of any condition associated with hypoxemia, dehydration, or sepsis. Because impaired hepatic function may significantly limit the ability to clear lactate, metformin hydrochloride extended-release tablets should generally be avoided in patients with clinical or laboratory evidence of hepatic disease. Patients should be cautioned against excessive alcohol intake, either acute or chronic, when taking metformin hydrochloride extended-release tablets, since alcohol potentiates the effects of metformin hydrochloride on lactate metabolism. In addition, metformin hydrochloride extended-release tablets should be temporarily discontinued prior to any intravascular radiocontrast study and for any surgical procedure (see also PRECAUTIONS).
The onset of lactic acidosis often is subtle, and accompanied only by nonspecific symptoms such as malaise, myalgias, respiratory distress, increasing somnolence, and nonspecific abdominal distress.There may be associated hypothermia, hypotension, and resistant bradyarrhythmias with more marked acidosis. The patient and the patient's physician must be aware of the possible importance of such symptoms and the patient should be instructed to notify the physician immediately if they occur (see also PRECAUTIONS). Metformin hydrochloride extended-release tablets should be withdrawn until the situation is clarified. Serum electrolytes, ketones, blood glucose, and if indicated, blood pH, lactate levels, and even blood metformin levels may be useful. Once a patient is stabilized on any dose level of metformin hydrochloride extended-release tablets, gastrointestinal symptoms, which are common during initiation of therapy, are unlikely to be drug related. Later occurrence of gastrointestinal symptoms could be due to lactic acidosis or other serious disease.
Levels of fasting venous plasma lactate above the upper limit of normal but less than 5 mmol/L in patients taking metformin hydrochloride extended-release tablets do not necessarily indicate impending lactic acidosis and may be explainable by other mechanisms, such as poorly controlled diabetes or obesity, vigorous physical activity, or technical problems in sample handling. (See also PRECAUTIONS.)
Lactic acidosis should be suspected in any diabetic patient with metabolic acidosis lacking evidence of ketoacidosis (ketonuria and ketonemia).
Lactic acidosis is a medical emergency that must be treated in a hospital setting. In a patient with lactic acidosis who is taking metformin hydrochloride extended-release tablets, the drug should be discontinued immediately and general supportive measures promptly instituted. Because metformin hydrochloride is dialyzable (with a clearance of up to 170 mL/min under good hemodynamic conditions), prompt hemodialysis is recommended to correct the acidosis and remove the accumulated metformin. Such management often results in prompt reversal of symptoms and recovery.